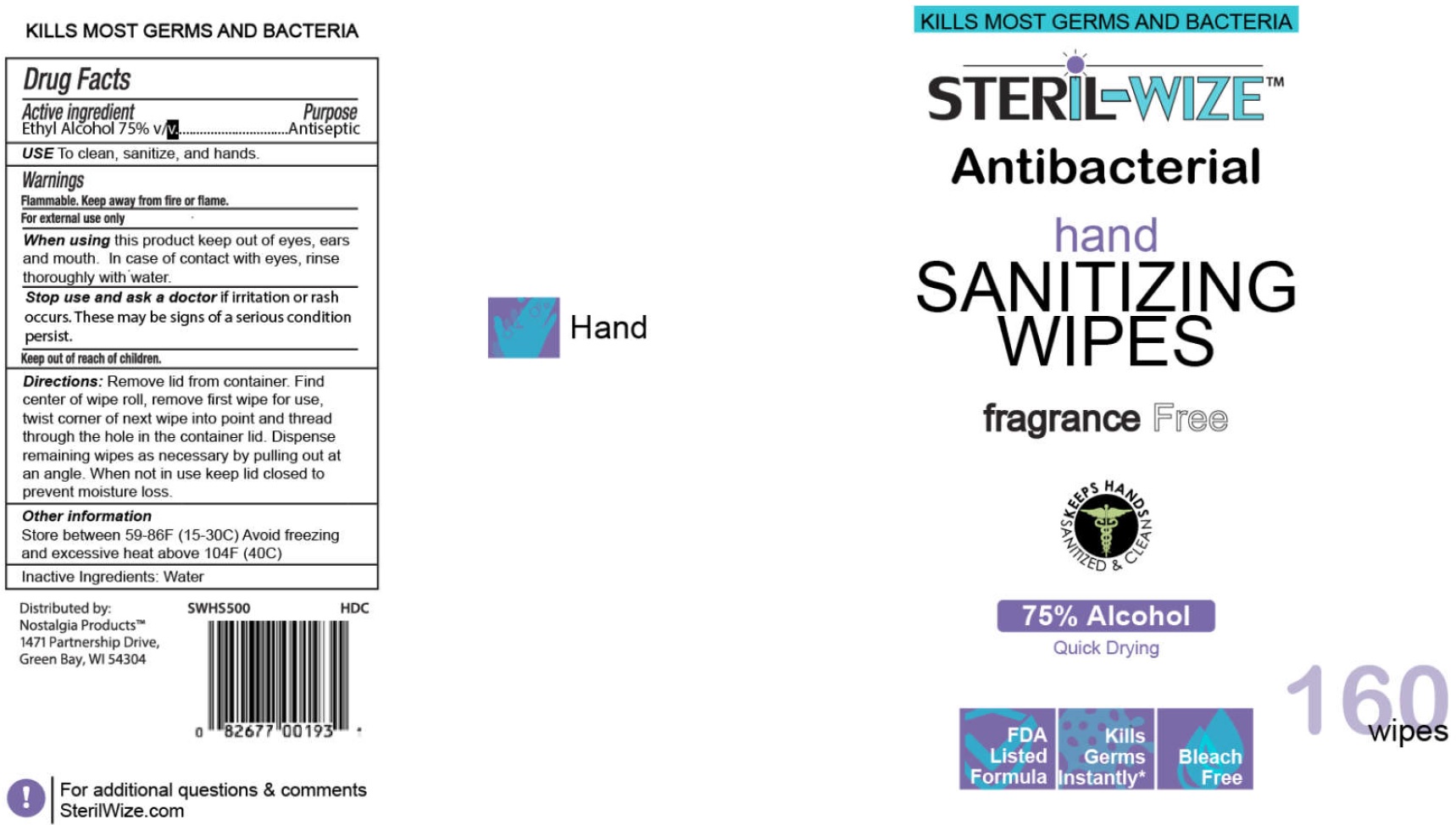 DRUG LABEL: Steril-Wize Antibacterial Hand Sanitizing Wipes, Fragrance Free
NDC: 77051-005 | Form: CLOTH
Manufacturer: Nostalgia Products LLC
Category: otc | Type: HUMAN OTC DRUG LABEL
Date: 20200928

ACTIVE INGREDIENTS: ALCOHOL 0.75 mL/1 mL
INACTIVE INGREDIENTS: WATER

Steril-Wize Antibacterial Hand Sanitizing Wipes, Fragrance Free

Active ingredient

Ethyl Alcohol 75% v/v

Purpose

Antiseptic

USE

To clean, sanitize, and hands.

Warnings

Flammable, Keep away from fire or flame.

For external use only

When using this product

keep out of eyes, ears and mouth. In case of contact with eyes, rinse thoroughly with water.

Stop use and ask a doctor

if irritation or rash occurs. These may be signs of a serious condition persist.

Directions:

Remove lid from container. Find center of wipe roll, remove first wipe for use, twist corner of next wipe into point and thread through the hole in the container lid. Dispense remaining wipes as necessary by pulling out at an angle. When not in use keep lid closed to prevent moisture loss.

Other information

Store between 59-86F (15-30C) Avoid freezing and excessive heat above 104F (40C)

Inactive Ingredients:

Water